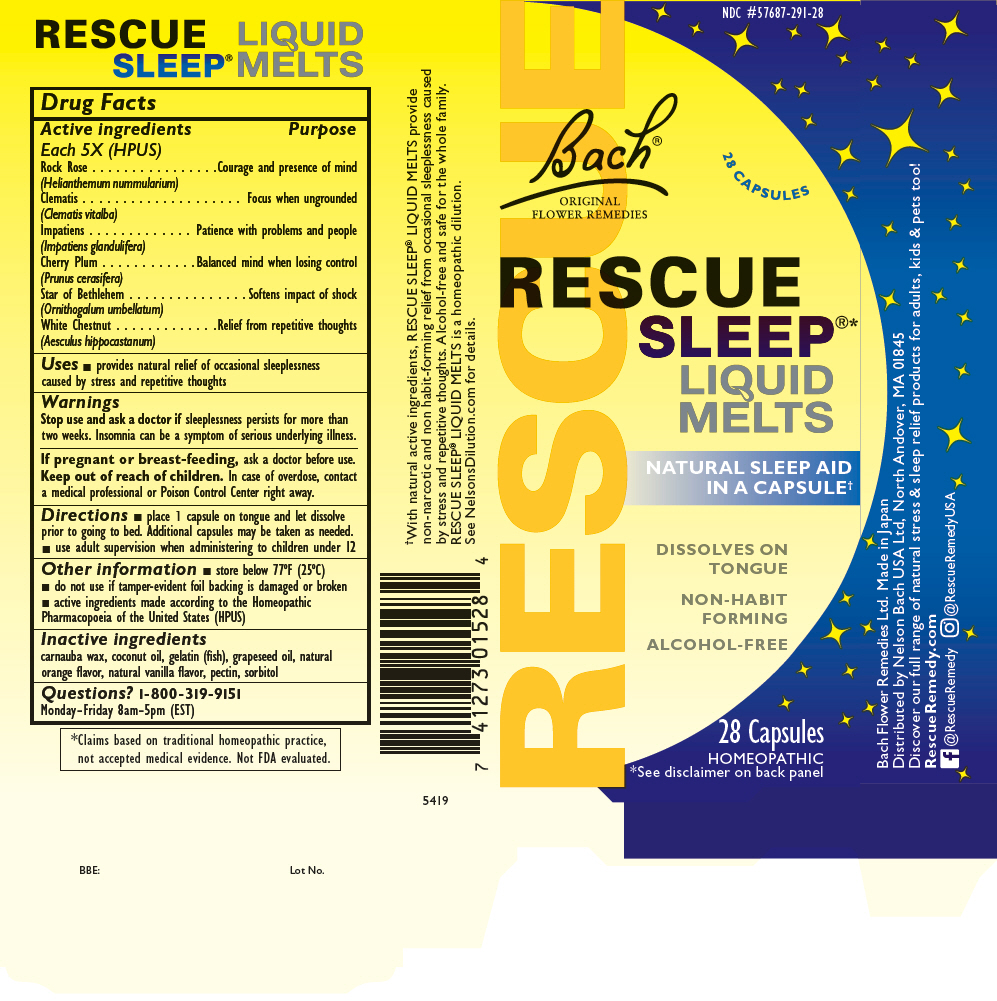 DRUG LABEL: Rescue Sleep
NDC: 57687-291 | Form: CAPSULE, LIQUID FILLED
Manufacturer: Nelson Bach USA, Ltd.
Category: homeopathic | Type: HUMAN OTC DRUG LABEL
Date: 20221006

ACTIVE INGREDIENTS: HELIANTHEMUM NUMMULARIUM FLOWER 5 [hp_X]/1 1; CLEMATIS VITALBA FLOWER 5 [hp_X]/1 1; IMPATIENS GLANDULIFERA FLOWER 5 [hp_X]/1 1; PRUNUS CERASIFERA FLOWER 5 [hp_X]/1 1; ORNITHOGALUM UMBELLATUM WHOLE 5 [hp_X]/1 1; AESCULUS HIPPOCASTANUM FLOWER 5 [hp_X]/1 1
INACTIVE INGREDIENTS: CARNAUBA WAX; COCONUT OIL; MARINE NON-GELLING GELATIN, HIGH MW; GRAPE SEED OIL; ORANGE OIL; VANILLA BEAN; PECTIN; SORBITOL

RESCUE®
SLEEP
LIQUID
MELTS

Drug Facts

ACTIVE INGREDIENT

Active ingredients Each 5X (HPUS) | Purpose
Rock Rose (Helianthemum nummularium) | Courage and presence of mind
Clematis (Clematis vitalba) | Focus when ungrounded
Impatiens (Impatiens glandulifera) | Patience with problems and people
Cherry Plum (Prunus cerasifera) | Balanced mind when losing control
Star of Bethlehem (Ornithogalum umbellatum) | Softens impact of shock
White Chestnut (Aesculus hippocastanum) | Relief from repetitive thoughts

Uses

- provides natural relief of occasional sleeplessness caused by stress and repetitive thoughts

Warnings

Stop use and ask a doctor if sleeplessness persists for more than two weeks. Insomnia can be a symptom of serious underlying illness.

PREGNANCY OR BREAST FEEDING

If pregnant or breast-feeding, ask a doctor before use.

Keep out of reach of children. In case of overdose, contact a medical professional or Poison Control Center right away.

Directions

- place 1 capsule on tongue and let dissolve prior to going to bed. Additional capsules may be taken as needed.
- use adult supervision when administering to children under 12

Other information

- store below 77°F (25°C)
- do not use if tamper-evident foil backing is damaged or broken
- active ingredients made according to the Homeopathic Pharmacopoeia of the United States (HPUS)

Inactive ingredients

carnauba wax, coconut oil, gelatin (fish), grapeseed oil, natural orange flavor, natural vanilla flavor, pectin, sorbitol

Questions?

1-800-319-9151
Monday-Friday 8am-5pm (EST)

Distributed by Nelson Bach USA Ltd, North Andover, MA 01845

PRINCIPAL DISPLAY PANEL - 28 Capsule Blister Pack Carton

NDC #57687-291-28

Bach®
ORIGINAL
FLOWER REMEDIES

28 CAPSULES

RESCUE
SLEEP®*
LIQUID
MELTS

NATURAL SLEEP AID
IN A CAPSULE†

DISSOLVES ON
TONGUE

NON-HABIT
FORMING

ALCOHOL-FREE

28 Capsules

HOMEOPATHIC
*See disclaimer on back panel